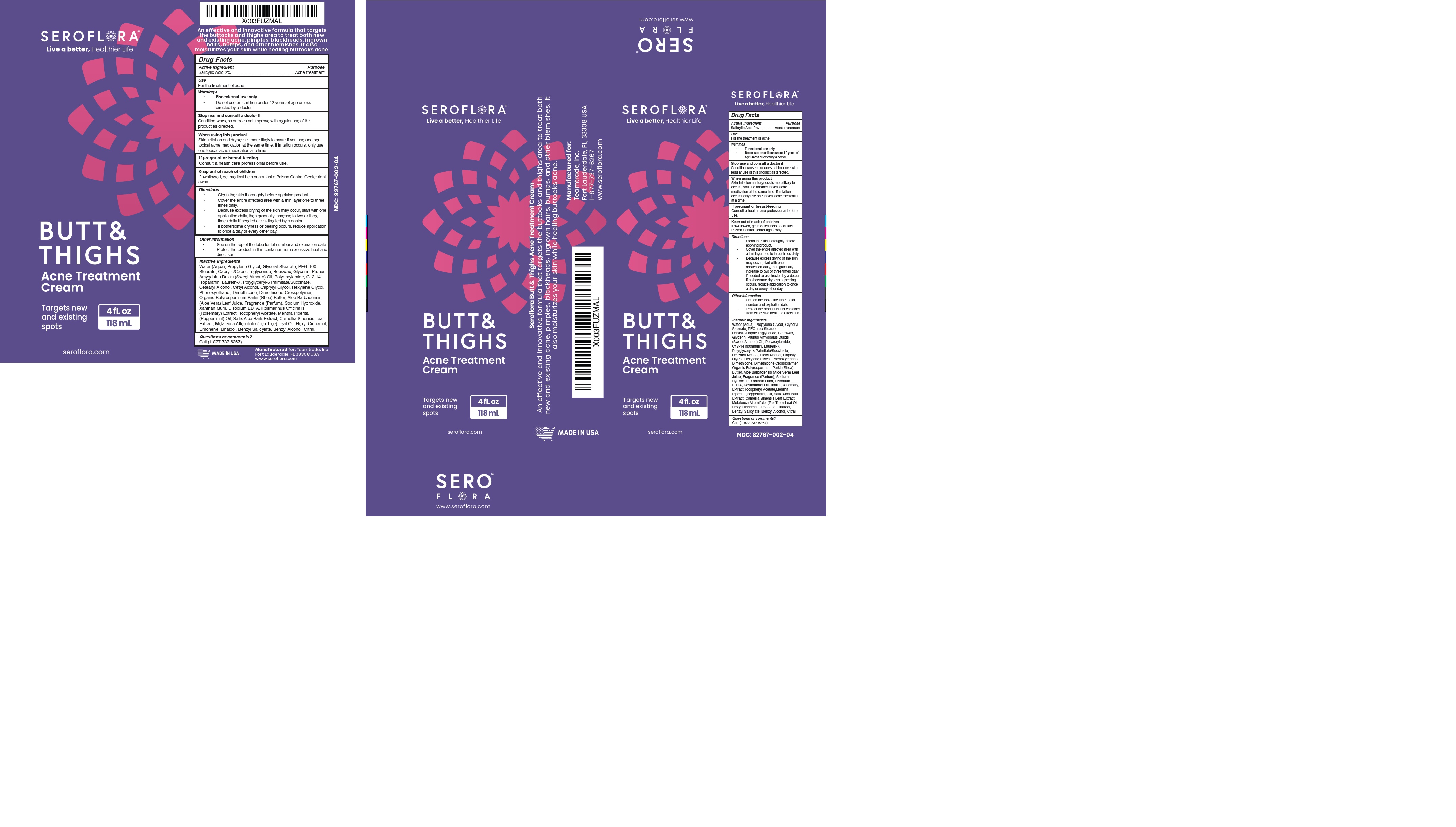 DRUG LABEL: BUTT AND THIGHS
NDC: 82767-002 | Form: CREAM
Manufacturer: Teamtrade Inc.
Category: otc | Type: HUMAN OTC DRUG LABEL
Date: 20231018

ACTIVE INGREDIENTS: SALICYLIC ACID 2 g/100 mL
INACTIVE INGREDIENTS: DIMETHICONE/DIENE DIMETHICONE CROSSPOLYMER; POLYGLYCERIN-6; GREEN TEA LEAF; PHENOXYETHANOL; CETOSTEARYL ALCOHOL; ALMOND OIL; CETYL ALCOHOL; SHEA BUTTER; XANTHAN GUM; PROPYLENE GLYCOL; LAURETH-7; GLYCERIN; CAPRYLYL GLYCOL; EDETATE DISODIUM; .ALPHA.-TOCOPHEROL ACETATE; C13-14 ISOPARAFFIN; HEXYLENE GLYCOL; LIMONENE, (+)-; ALOE VERA LEAF; TEA TREE OIL; MEDIUM-CHAIN TRIGLYCERIDES; WHITE WAX; GLYCERYL STEARATE/PEG-100 STEARATE; SODIUM HYDROXIDE; ROSEMARY; PEPPERMINT OIL; .ALPHA.-HEXYLCINNAMALDEHYDE; LINALOOL, (+/-)-; BENZYL SALICYLATE; BENZYL ALCOHOL; CITRAL; WATER; SALIX ALBA BARK

82767-002-04

ACTIVE INGREDIENT

Salicylic Acid 2%

Purpose: Acne treatment

USE:

For the treatment of acne.

WARNINGS

For external use only.

Do not use on children under 12 years of age unless directed by a doctor.

Stop use and consult a doctor if

Condition worsens or does not improve with regular use of this product as directed.

WHEN USING

Skin irritation and dryness is more likely to occur if you use another topical acne medication at the same time. If irritation occurs, only use one topical acne medication at a time.

PREGNANCY OR BREAST FEEDING

If pregnant or breast-feeding Consult a health care professional before use

KEEP OUT OF REACH OF CHILDREN

If swallowed, get medical help or contact a Poison Control Center right away.

DIRECTIONS:

Clean the skin thoroughly before applying product.
Cover the entire affected area with a thin layer one to three times daily.
Because excess drying of the skin may occur, start with one application daily, then gradually increase to two or three times daily if needed or as directed by a doctor.

If bothersome dryness or peeling occurs, reduce application to once a day or every other day.

OTHER SAFETY INFORMATION

See on the top of the tube for lot number and expiration date.

Protect the product in this container from excessive heat and direct sun.

INACTIVE INGREDIENT

Aqua, Propylene Glycol, Glyceryl Stearate, PEG-100 Stearate, Caprylic/Capric Triglyceride, Beeswax, Glycerin, Polyglyceryl-6 Palmitate/Succinate, Cetearyl Alcohol, Prunus Amygdalus Dulcis (Sweet Almond) Oil, Polyacrylamide, C13-14 Isoparaffin, Laureth-7, Cetyl Alcohol, Caprylyl Glycol, Hexylene Glycol, Phenoxyethanol, Organic Butyrospermum Parkii (Shea) Butter, Dimethicone, Dimethicone Crosspolymer, Aloe Barbadensis (Aloe Vera) Leaf Juice, Parfum, Sodium Hydroxide, Xanthan Gum, Disodium EDTA, Rosmarinus Officinalis (Rosemary) Extract, Tocopheryl Acetate, Mentha Piperita (Peppermint) Oil, Salix Alba Bark Extract, Camellia Sinensis Leaf Extract, Melaleuca Alternifolia (Tea Tree) Leaf Oil, Hexyl Cinnamal, D-Limonene, Linalool, Benzyl Salicylate, Benzyl Alcohol, Citral.

QUESTIONS

Call (1-877-737-6267)